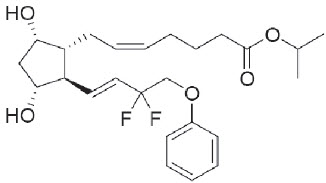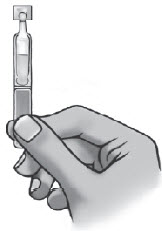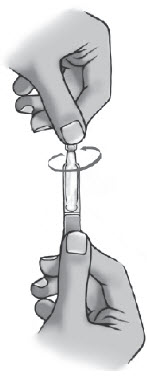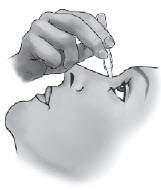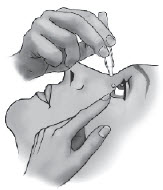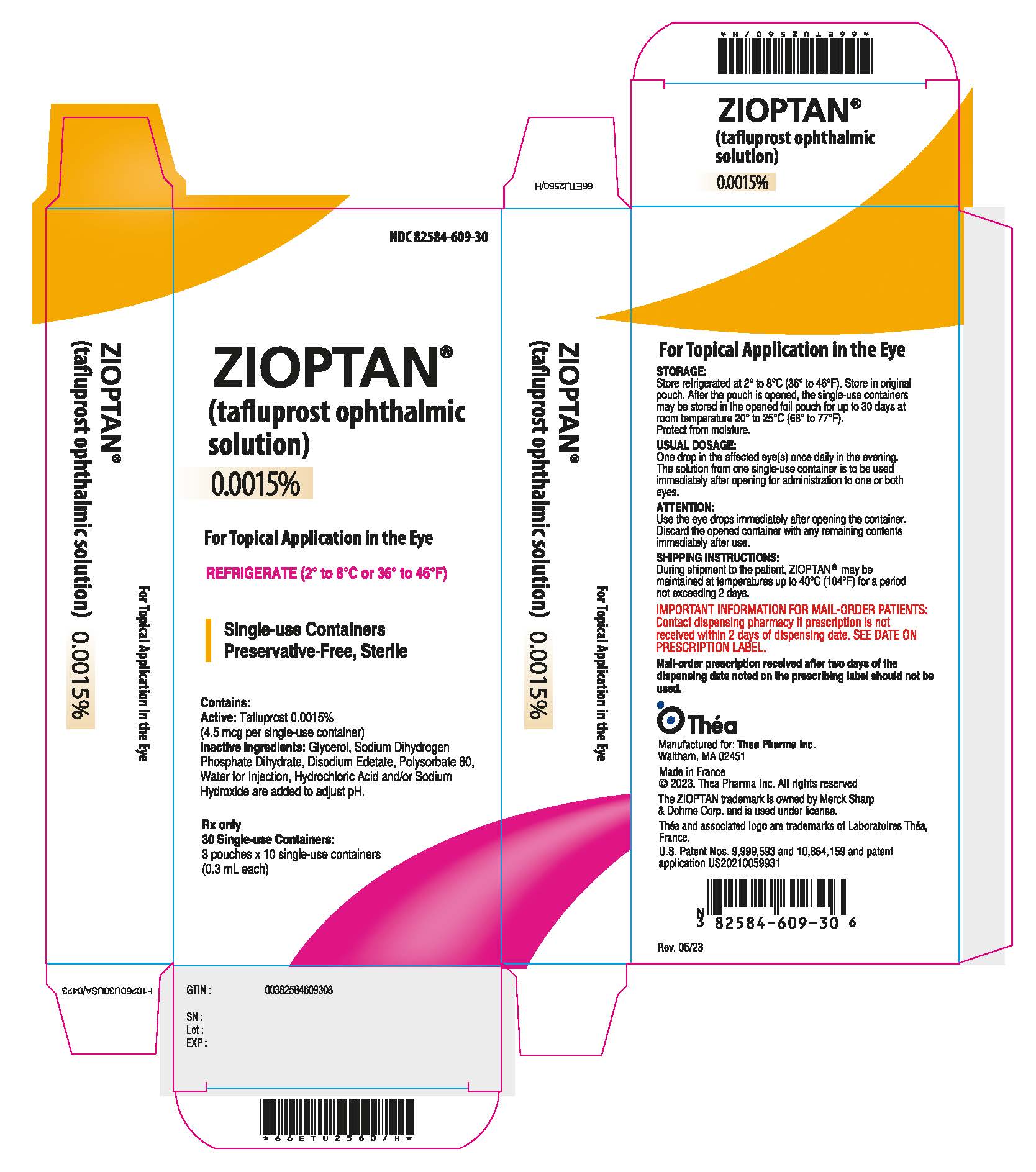 DRUG LABEL: ZIOPTAN
NDC: 82584-609 | Form: SOLUTION/ DROPS
Manufacturer: Thea Pharma Inc.
Category: prescription | Type: HUMAN PRESCRIPTION DRUG LABEL
Date: 20240417

ACTIVE INGREDIENTS: TAFLUPROST 0.015 mg/1 mL
INACTIVE INGREDIENTS: GLYCERIN; SODIUM PHOSPHATE, MONOBASIC, DIHYDRATE; EDETATE DISODIUM; POLYSORBATE 80; WATER; HYDROCHLORIC ACID; SODIUM HYDROXIDE

HIGHLIGHTS OF PRESCRIBING INFORMATION

These highlights do not include all the information needed to use ZIOPTAN® (tafluprost ophthalmic solution) 0.0015% safely and effectively. See full prescribing information for ZIOPTAN®.
ZIOPTAN® (tafluprost ophthalmic solution) 0.0015%
Initial U.S. Approval: 2012

1 INDICATIONS AND USAGE

- ZIOPTAN® (tafluprost ophthalmic solution) 0.0015% is a prostaglandin analog indicated for reducing elevated intraocular pressure in patients with open-angle glaucoma or ocular hypertension. (1)

2 DOSAGE AND ADMINISTRATION

- One drop in the affected eye(s) once daily in the evening. (2)

3 DOSAGE FORMS AND STRENGTHS

- Ophthalmic solution containing tafluprost 0.015 mg/mL (3)

4 CONTRAINDICATIONS

- None. (4)

5 WARNINGS AND PRECAUTIONS

- Pigmentation

Pigmentation of the iris, periorbital tissue (eyelid) and eyelashes can occur. Iris pigmentation is likely to be permanent. (5.1)

- Eyelash Changes

Gradual changes to eyelashes including increased length, thickness and number of lashes. Usually reversible. (5.2)

6 ADVERSE REACTIONS

- Most common ocular adverse reaction is conjunctival hyperemia (range 4% to 20%). (6.1)

To report SUSPECTED ADVERSE REACTIONS, contact Thea Pharma Inc. at 1-833-838-4028 or FDA at 1-800-FDA-1088 or www.fda.gov/medwatch.

8 USE IN SPECIFIC POPULATIONS

- Use in pediatric patients is not recommended because of potential safety concerns related to increased pigmentation following long-term chronic use. (8.4)

FULL PRESCRIBING INFORMATION

1 INDICATIONS AND USAGE

ZIOPTAN® (tafluprost ophthalmic solution) 0.0015% is indicated for reducing elevated intraocular pressure in patients with open-angle glaucoma or ocular hypertension.

2 DOSAGE AND ADMINISTRATION

The recommended dose is one drop of ZIOPTAN® in the conjunctival sac of the affected eye(s) once daily in the evening.

The dose should not exceed once daily since it has been shown that more frequent administration of prostaglandin analogs may lessen the intraocular pressure lowering effect.

Reduction of the intraocular pressure starts approximately 2 to 4 hours after the first administration with the maximum effect reached after 12 hours.

ZIOPTAN® may be used concomitantly with other topical ophthalmic drug products to lower intraocular pressure. If more than one topical ophthalmic product is being used, each one should be administered at least 5 minutes apart.

The solution from one individual unit is to be used immediately after opening for administration to one or both eyes. Since sterility cannot be maintained after the individual unit is opened, the remaining contents should be discarded immediately after administration.

3 DOSAGE FORMS AND STRENGTHS

Ophthalmic solution containing tafluprost 0.015 mg/mL.

4 CONTRAINDICATIONS

None.

5 WARNINGS AND PRECAUTIONS

5.1 Pigmentation

Tafluprost ophthalmic solution has been reported to cause changes to pigmented tissues. The most frequently reported changes have been increased pigmentation of the iris, periorbital tissue (eyelid) and eyelashes. Pigmentation is expected to increase as long as tafluprost is administered. The pigmentation change is due to increased melanin content in the melanocytes rather than to an increase in the number of melanocytes. After discontinuation of tafluprost, pigmentation of the iris is likely to be permanent, while pigmentation of the periorbital tissue and eyelash changes have been reported to be reversible in some patients. Patients who receive treatment should be informed of the possibility of increased pigmentation. The long term effects of increased pigmentation are not known.

Iris color change may not be noticeable for several months to years. Typically, the brown pigmentation around the pupil spreads concentrically towards the periphery of the iris and the entire iris or parts of the iris become more brownish. Neither nevi nor freckles of the iris appear to be affected by treatment. While treatment with ZIOPTAN® can be continued in patients who develop noticeably increased iris pigmentation, these patients should be examined regularly. [See Patient Counseling Information (17.3)].

5.2 Eyelash Changes

ZIOPTAN® may gradually change eyelashes and vellus hair in the treated eye. These changes include increased length, color, thickness, shape and number of lashes. Eyelash changes are usually reversible upon discontinuation of treatment.

5.3 Intraocular Inflammation

ZIOPTAN® should be used with caution in patients with active intraocular inflammation (e.g., iritis/uveitis) because the inflammation may be exacerbated.

5.4 Macular Edema

Macular edema, including cystoid macular edema, has been reported during treatment with prostaglandin F2α analogs. ZIOPTAN® should be used with caution in aphakic patients, in pseudophakic patients with a torn posterior lens capsule, or in patients with known risk factors for macular edema.

6 ADVERSE REACTIONS

6.1 Clinical Studies Experience

Because clinical studies are conducted under widely varying conditions, adverse reaction rates observed in the clinical studies of a drug cannot be directly compared to rates in the clinical studies of another drug and may not reflect the rates observed in practice.

Preservative-containing or preservative-free tafluprost 0.0015% was evaluated in 905 patients in five controlled clinical studies of up to 24-months duration. The most common adverse reaction observed in patients treated with tafluprost was conjunctival hyperemia which was reported in a range of 4% to 20% of patients. Approximately 1% of patients discontinued therapy due to ocular adverse reactions.

Ocular adverse reactions reported at an incidence of ≥ 2% in these clinical studies included ocular stinging/irritation (7%), ocular pruritus including allergic conjunctivitis (5%), cataract (3%), dry eye (3%), ocular pain (3%), eyelash darkening (2%), growth of eyelashes (2%) and vision blurred (2%).

Nonocular adverse reactions reported at an incidence of 2% to 6% in these clinical studies in patients treated with tafluprost 0.0015% were headache (6%), common cold (4%), cough (3%) and urinary tract infection (2%).

6.2 Postmarketing Experience

The following adverse reactions have been identified during postapproval use of tafluprost. Because postapproval adverse reactions are reported voluntarily from a population of uncertain size, it is not always possible to reliably estimate their frequency or establish a causal relationship to drug exposure.

Respiratory disorders: exacerbation of asthma, dyspnea

Eye disorders: iritis/uveitis

In postmarketing use with prostaglandin analogs, periorbital and lid changes including deepening of the eyelid sulcus have been observed.

8 USE IN SPECIFIC POPULATIONS

8.1 Pregnancy

Pregnancy Category C.

TERATOGENIC EFFECTS

Teratogenic effects: In embryo-fetal development studies in rats and rabbits, tafluprost administered intravenously was teratogenic. Tafluprost caused increases in post-implantation losses in rats and rabbits and reductions in fetal body weights in rats. Tafluprost also increased the incidence of vertebral skeletal abnormalities in rats and the incidence of skull, brain and spine malformations in rabbits. In rats, there were no adverse effects on embryo-fetal development at a dose of 3 mcg/kg/day corresponding to maternal plasma levels of tafluprost acid that were 343 times the maximum clinical exposure based on Cmax. In rabbits, effects were seen at a tafluprost dose of 0.03 mcg/kg/day corresponding to maternal plasma levels of tafluprost acid during organogenesis that were approximately 5 times higher than the clinical exposure based on Cmax. At the no-effect dose in rabbits (0.01 mcg/kg/day), maternal plasma levels of tafluprost acid were below the lower level of quantification (20 pg/mL).

In a pre- and postnatal development study in rats, increased mortality of newborns, decreased body weights and delayed pinna unfolding were observed in offsprings. The no observed adverse effect level was at a tafluprost intravenous dose of 0.3 mcg/kg/day which is greater than 3 times the maximum recommended clinical dose based on body surface area comparison.

There are no adequate and well-controlled studies in pregnant woman. Although animal reproduction studies are not always predictive of human response, ZIOPTAN® should not be used during pregnancy unless the potential benefit justifies the potential risk to the fetus.

Women of childbearing age/potential should have adequate contraceptive measures in place.

8.3 Nursing Mothers

A study in lactating rats demonstrated that radio-labeled tafluprost and/or its metabolites were excreted in milk. It is not known whether this drug or its metabolites are excreted in human milk. Because many drugs are excreted in human milk, caution should be exercised when ZIOPTAN® is administered to a nursing woman.

8.4 Pediatric Use

Use in pediatric patients is not recommended because of potential safety concerns related to increased pigmentation following long-term chronic use.

8.5 Geriatric Use

No overall clinical differences in safety or effectiveness have been observed between elderly and other adult patients.

11 DESCRIPTION

Tafluprost is a fluorinated analog of prostaglandin F2α. The chemical name for tafluprost is 1-methylethyl (5Z)-7-{(1R,2R,3R,5S)-2-[(1E)-3,3-difluoro-4-phenoxy-1-butenyl}-3,5-dihydroxycyclopen t y l]-5-heptenoate. The molecular formula of tafluprost is C25H34F2O5 and its molecular weight is 452.53.

Its structural formula is:

Tafluprost is a colorless to light yellow viscous liquid that is practically insoluble in water.

ZIOPTAN® (tafluprost ophthalmic solution) 0.0015% is supplied as a sterile solution of tafluprost with a pH range of 5.5 to 6.7 and an Osmolality range of 260 to 300 mOsmo/kg.

ZIOPTAN® contains Active: tafluprost 0.015 mg/mL; Inactives: glycerol, sodium dihydrogen phosphate dihydrate, disodium edetate, polysorbate 80, hydrochloric acid and/or sodium hydroxide (to adjust pH) and Water for Injection.

ZIOPTAN® does not contain a preservative.

12 CLINICAL PHARMACOLOGY

12.1 Mechanism of Action

Tafluprost acid, a prostaglandin analog is a selective FP prostanoid receptor agonist which is believed to reduce intraocular pressure by increasing uveoscleral outflow. The exact mechanism of action is unknown at this time.

12.3 Pharmacokinetics

Absorption

Following instillation, tafluprost is absorbed through the cornea and is hydrolyzed to the biologically active acid metabolite, tafluprost acid. Following instillation of one drop of the 0.0015% solution once daily into each eye of healthy volunteers, the plasma concentrations of tafluprost acid peaked at a median time of 10 minutes on both Days 1 and 8. The mean plasma Cmax of tafluprost acid were 26 pg/mL and 27 pg/mL on Day 1, and Day 8, respectively. The mean plasma AUC estimates of tafluprost acid were 394 pg*min/mL and 432 pg*min/mL on day 1 and 8, respectively.

Metabolism

Tafluprost, an ester prodrug, is hydrolyzed to its biologically active acid metabolite in the eye. The acid metabolite is further metabolized via fatty acid β-oxidation and phase II conjugation.

Elimination

Mean plasma tafluprost acid concentrations were below the limit of quantification of the bioanalytical assay (10 pg/mL) at 30 minutes following topical ocular administration of tafluprost 0.0015% ophthalmic solution.

13 NONCLINICAL TOXICOLOGY

13.1 Carcinogenesis, Mutagenesis, Impairment of Fertility

Tafluprost was not carcinogenic when administered subcutaneously daily for 24 months at doses up to 30 mcg/kg/day in rats and for 18 months at doses up to 100 mcg/kg/day in mice (over 1600 and 1300 times, respectively, the maximum clinical exposure based on plasma AUC).

Tafluprost was not mutagenic or clastogenic in a battery of genetic toxicology studies, including an in vitro microbial mutagenesis assay, an in vitro chromosomal aberration assay in Chinese hamster lung cells, and an in vivo mouse micronucleus assay in bone marrow.

In rats, no adverse effects on mating performance or fertility were observed with intravenous dosing of tafluprost at a dose of 100 mcg/kg/day (over 14000 times the maximum clinical exposure based on plasma Cmax or over 3600 times based on plasma AUC).

14 CLINICAL STUDIES

In clinical studies up to 24 months in duration, patients with open-angle glaucoma or ocular hypertension and baseline pressure of 23 to 26 mmHg who were treated with ZIOPTAN® dosed once daily in the evening demonstrated reductions in intraocular pressure at 3 and 6 months of 6 to 8 mmHg and 5 to 8 mmHg, respectively.

16 HOW SUPPLIED/STORAGE AND HANDLING

ZIOPTAN® (tafluprost ophthalmic solution) 0.0015% is supplied as a sterile solution in translucent low density polyethylene single-use containers packaged in foil pouches (10 single-use containers per pouch). Each single-use container has 0.3 mL solution corresponding to 0.0045 mg tafluprost.

NDC 82584-609-30; Unit-of-Use Carton of 30.

Storage:

Store refrigerated at 2° to 8°C (36° to 46°F).

During shipment ZIOPTAN® may be maintained at temperatures up to 40°C (104°F) for a period not exceeding 2 days. Mail-order prescriptions received after two days of the dispensing date noted in the prescribing label should not be used. Store in the original pouch. After the pouch is opened, the single-use containers may be stored in the opened foil pouch for up to 30 days at room temperature 20° to 25°C (68° to 77°F). Protect from moisture. Write down the date you open the foil pouch in the space provided on the pouch. Discard any unused containers 30 days after first opening the pouch.

17 PATIENT COUNSELING INFORMATION

See FDA-Approved Patient Labeling (Patient Information).

17.1 Nightly Application

Advise patients to not exceed once daily dosing since more frequent administration may decrease the intraocular pressure lowering effect of ZIOPTAN®.

17.2 Handling the Single-Use Container

Advise patients that ZIOPTAN® is a sterile solution that does not contain a preservative. The solution from one individual unit is to be used immediately after opening for administration to one or both eyes. Since sterility cannot be maintained after the individual unit is opened, the remaining contents should be discarded immediately after administration.

17.3 Potential for Pigmentation

Advise patients about the potential for increased brown pigmentation of the iris, which may be permanent. Also inform patients about the possibility of eyelid skin darkening, which may be reversible after discontinuation of ZIOPTAN®.

17.4 Potential for Eyelash Changes

Inform patients of the possibility of eyelash and vellus hair changes in the treated eye during treatment with ZIOPTAN®. These changes may result in a disparity between eyes in length, thickness, pigmentation, number of eyelashes or vellus hairs, and/or direction of eyelash growth. Eyelash changes are usually reversible upon discontinuation of treatment.

17.5 When to Seek Physician Advice

Advise patients that if they develop a new ocular condition (e.g., trauma or infection), experience a sudden decrease in visual acuity, have ocular surgery, or develop any ocular reactions, particularly conjunctivitis and eyelid reactions, they should immediately seek their physician's advice concerning the continued use of ZIOPTAN®.

17.6 Use with Other Ophthalmic Drugs

If more than one topical ophthalmic drug is being used, the drugs should be administered at least five (5) minutes between applications.

17.7 Storage Information

Instruct patients on proper storage of cartons, unopened foil pouches, and opened foil pouches [see How Supplied/Storage and Handling (16)]. Recommended storage for cartons and unopened foil pouches is to store refrigerated at 2° to 8°C (36° to 46°F). After the pouch is opened, the single-use containers may be stored in the opened foil pouch for up to 30 days at room temperature 20° to 25°C (68° to 77°F). Protect from moisture.

Manufactured for : Thea Pharma Inc.

Waltham, MA 02451

Made in France
© 2023. Thea Pharma Inc. All rights reserved
The ZIOPTAN trademark is owned by Merck Sharp & Dohme Corp. and is used under license.

Théa and associated logo are trademarks of Laboratoires Théa, France.

U.S. Patent Nos. 9,999,593 and 10,864,159 and patent application US20210059931.

Rev. 05/2023

PATIENT INFORMATION

ZIOPTAN® (zye OP tan)
(tafluprost ophthalmic solution) 0.0015%

Read this Patient Information before you start using ZIOPTAN® and each time you get a refill. There may be new information. This information does not take the place of talking to your doctor about your medical condition or your treatment.

What is ZIOPTAN®?

ZIOPTAN® is a prescription sterile eye drop solution. ZIOPTAN® is used to lower the pressure in the eye (intraocular pressure) in people with open-angle glaucoma or ocular hypertension when their eye pressure is too high. ZIOPTAN® belongs to a group of medicines called prostaglandin analogs.

ZIOPTAN® is not for use in children.

What should I tell my doctor before using ZIOPTAN®?

Before you use ZIOPTAN®, tell your doctor if you:

- have or have had eye problems including any surgery on your eye or eyes
- are using any other eye medicines
- have any other medical problems
- are pregnant or plan to become pregnant. It is not known if ZIOPTAN® will harm your unborn baby. You should use an effective method of birth control while you use ZIOPTAN®. If you become pregnant while using ZIOPTAN® talk to your doctor right away.
- are breastfeeding or plan to breastfeed. It is not known if ZIOPTAN® passes into your breast milk. Talk to your doctor about the best way to feed your baby if you use ZIOPTAN®.

Tell your doctor about all the medicines you take, including prescription and non-prescription medicines, vitamins, and herbal supplements.

Know the medicines you take. Keep a list of them to show your doctor and pharmacist when you get a new medicine.

How should I take ZIOPTAN®?

Read the Instructions for Use at the end of this Patient Information leaflet for additional instructions about the right way to use ZIOPTAN®.

- Use 1 drop of ZIOPTAN® in your eye (or eyes) each evening. Talk to your doctor or pharmacist if you are not sure how to use ZIOPTAN®.
- Your ZIOPTAN® may not work as well if you use it more than 1 time each evening.
- If you use other medicines in your eye, wait at least 5 minutes between using ZIOPTAN® and your other eye medicines.
- Use your ZIOPTAN® right away after opening. Each ZIOPTAN® single-use container is sterile and is to be used 1 time then thrown away. Do not save any ZIOPTAN® that may be left over after you use your medicine. Using ZIOPTAN® that is not sterile may cause other eye problems.

What are the possible side effects of ZIOPTAN®?

ZIOPTAN® may cause serious side effects including:

- changes in the color of your eye (iris). Your iris may become more brown in color while using ZIOPTAN®. This color change may not go away when you stop using ZIOPTAN®. If ZIOPTAN® is used in 1 eye only, the color of that eye may always be a different color from the color of your other eye.
- darkening of the color of the skin around your eye (eyelid). These skin changes usually go away when you stop using ZIOPTAN®.
- increasing the length, thickness, color, or number of your eyelashes. These eyelash changes usually go away when you stop using ZIOPTAN®.
- hair growth on your eyelids. This hair growth usually goes away when you stop using ZIOPTAN®.

The most common side effects of ZIOPTAN® include:

- redness, stinging or itching of your eye
- cataract formation
- dry eye
- eye pain
- blurred vision
- headache
- common cold
- cough
- urinary tract infection

Tell your doctor if you have any new eye problems while using ZIOPTAN® including:

- an eye injury
- an eye infection
- a sudden loss of vision
- eye surgery
- swelling and redness of and around your eye (conjunctivitis)
- problems with your eyelids

Additionally, the following side effects have been reported in general use:

- worsening of asthma
- shortness of breath

Tell your doctor if you have any other side effects that bother you.

These are not all the possible side effects of ZIOPTAN®. For more information, ask your doctor or pharmacist.

Call your doctor for medical advice about side effects. You may report side effects to FDA at 1-800-FDA-1088.

How should I store ZIOPTAN®?

Important information for Mail-Order Patients:

Do not use if prescription is not received within two days of dispensing date.

Keep the foil pouches and ZIOPTAN® single-use containers dry.

Before opening the foil pouches:

- Store the unopened foil pouches in a refrigerator between 36°F to 46°F (2°C to 8°C).
- Do not open the pouch containing ZIOPTAN® until you are ready to use the eye drops.

After opening the foil pouch:

- Store the opened foil pouch at room temperature, between 68°F to 77°F (20°C to 25°C), for up to 30 days.
- Throw away all unused ZIOPTAN® single-use containers in the opened foil pouch after 30 days.
- Keep the ZIOPTAN® single-use containers in their original foil pouch.
- After opening the foil pouch, refrigeration is not required.

Keep ZIOPTAN® and all medicines out of the reach of children.

General information about the safe and effective use of ZIOPTAN®.

Do not use ZIOPTAN® for a condition for which it was not prescribed. Do not give ZIOPTAN® to other people, even if they have the same symptoms that you have. It may harm them.

This Patient Information leaflet summarizes the most important information about ZIOPTAN®. If you would like more information, talk with your doctor. You can ask your pharmacist or doctor for information about ZIOPTAN® that is written for health professionals.

What are the ingredients in ZIOPTAN®?

Active ingredients: tafluprost

Inactive ingredients: glycerol, sodium dihydrogen phosphate dihydrate, disodium edetate, and polysorbate 80, hydrochloric acid and/or sodium hydroxide, and water for injection.

Instructions for Use

Read these Instructions for Use before using your ZIOPTAN® and each time you get a refill. There may be new information. This leaflet does not take the place of talking with your doctor about your medical condition or your treatment.

Important:

- ZIOPTAN® is for the eye only. Do not swallow ZIOPTAN®.
- ZIOPTAN® single-use containers are packaged in a foil pouch.
- Do not use the ZIOPTAN® single-use containers if the foil pouch is opened.
- Write down the date you open the foil pouch in the space provided on the pouch.

Every time you use ZIOPTAN®:

Step 1. | Wash your hands.
Step 2. | Take the strip of single-use containers from the foil pouch.
Step 3. | Pull off one single-use container from the strip.
Step 4. | Put the remaining strip of single-use containers back in the foil pouch and fold the edge to close the pouch.
Step 5. | Hold the single-use container upright. Make sure that your ZIOPTAN® medicine is in the bottom part of the single-use container. See Figure A. | Figure A
Step 6. | Open the single-use container by twisting off the tab. See Figure B. | Figure B
Step 7. | Tilt your head backwards. If you are unable to tilt your head, lie down.
Step 8. | Place the tip of the single-use container close to your eye. Be careful not to touch your eye with the tip of the single-use container. See Figure C. | Figure C
Step 9. | Pull your lower eyelid downwards and look up.
Step 10. | Gently squeeze the container and let 1 drop of ZIOPTAN® fall into the space between your lower eyelid and your eye. If a drop misses your eye, try again. See Figure D. | Figure D

- If your doctor has told you to use ZIOPTAN® drops in both eyes, repeat Steps 7 to 10 for your other eye.
- There is enough ZIOPTAN® in one single-use container for both of your eyes.
- Throw away the opened single-use container with any remaining ZIOPTAN® right away.

This Patient Information and Instructions for Use have been approved by the U.S. Food and Drug Administration.

Rx only

Manufactured for : Thea Pharma Inc.

Waltham, MA 02451

Made in France
© 2023. Thea Pharma Inc. All rights reserved
The ZIOPTAN trademark is owned by Merck Sharp & Dohme Corp. and is used under license.

Revised: 05/2023

N10260U30USA/0423

Revised: 3/2024

Thea Pharma Inc.

PRINCIPAL DISPLAY PANEL - 0.3 mL Container Pouch Carton

NDC 82584-609-30

ZIOPTAN ®
(tafluprost ophthalmic
solution)
0.0015%

For Topical Application in the Eye

REFRIGERATE (2° to 8°C or 36° to 46°F)

Single-use Containers
Preservative-Free, Sterile

Contains:
Active: Tafluprost 0.0015%
(4.5 mcg per single-use container)
Inactive ingredients: Glycerol, Sodium Dihydrogen
Phosphate Dihydrate, Disodium Edetate, Polysorbate 80,
Water for Injection, Hydrochloric Acid and/or Sodium
Hydroxide are added to adjust pH.

Rx only
30 Single-use Containers:
3 pouches x 10 single-use containers
(0.3 mL each)